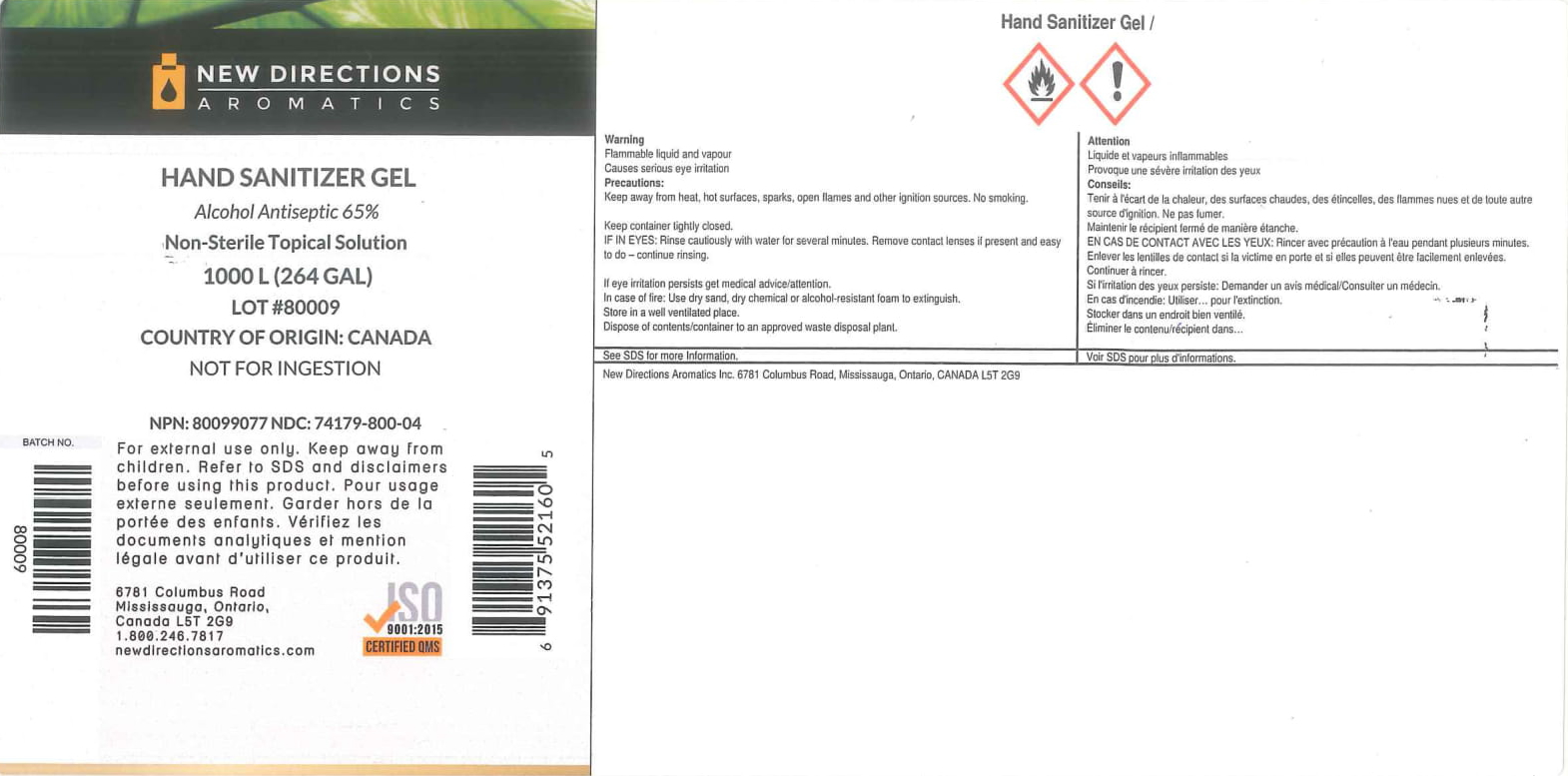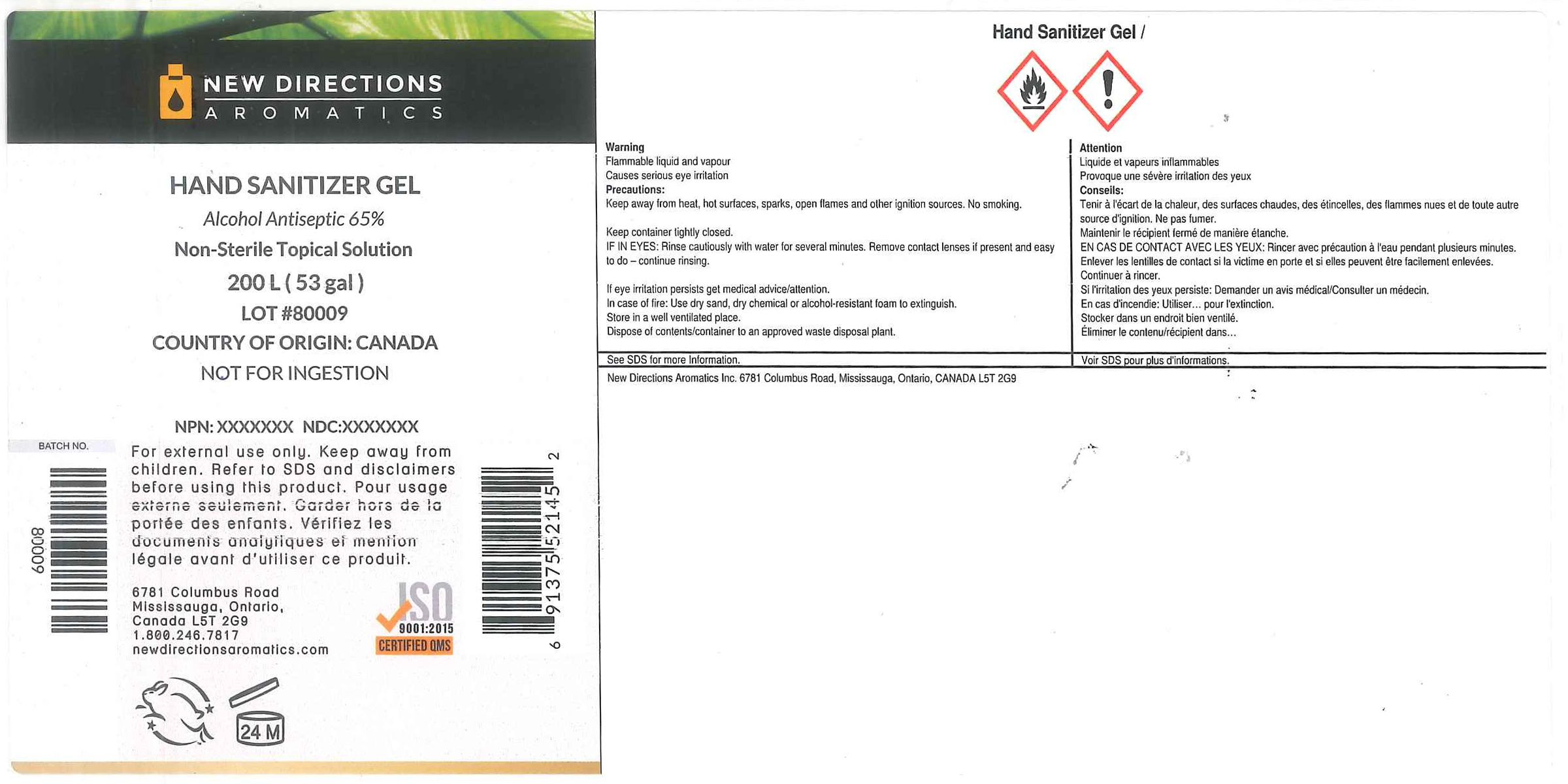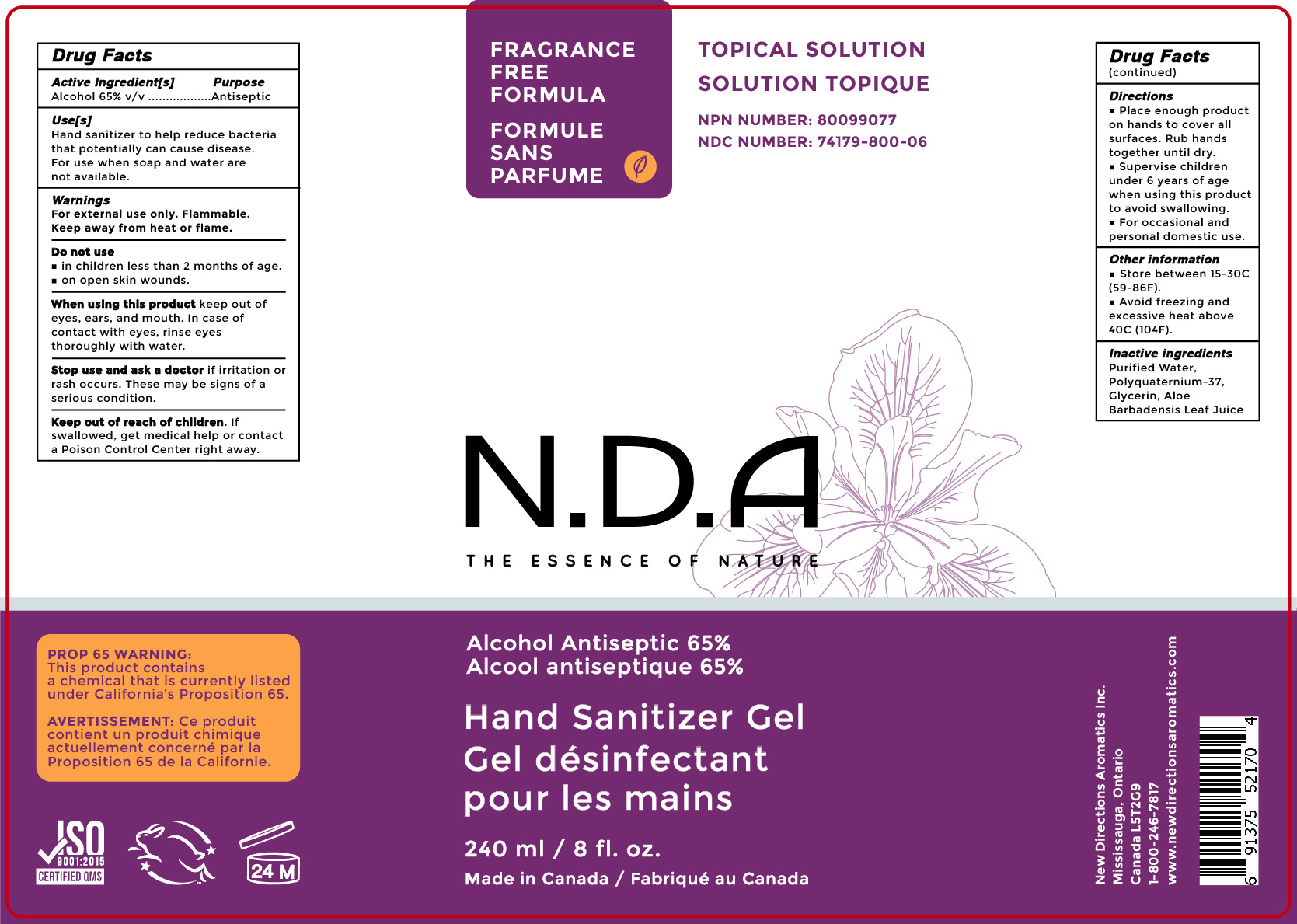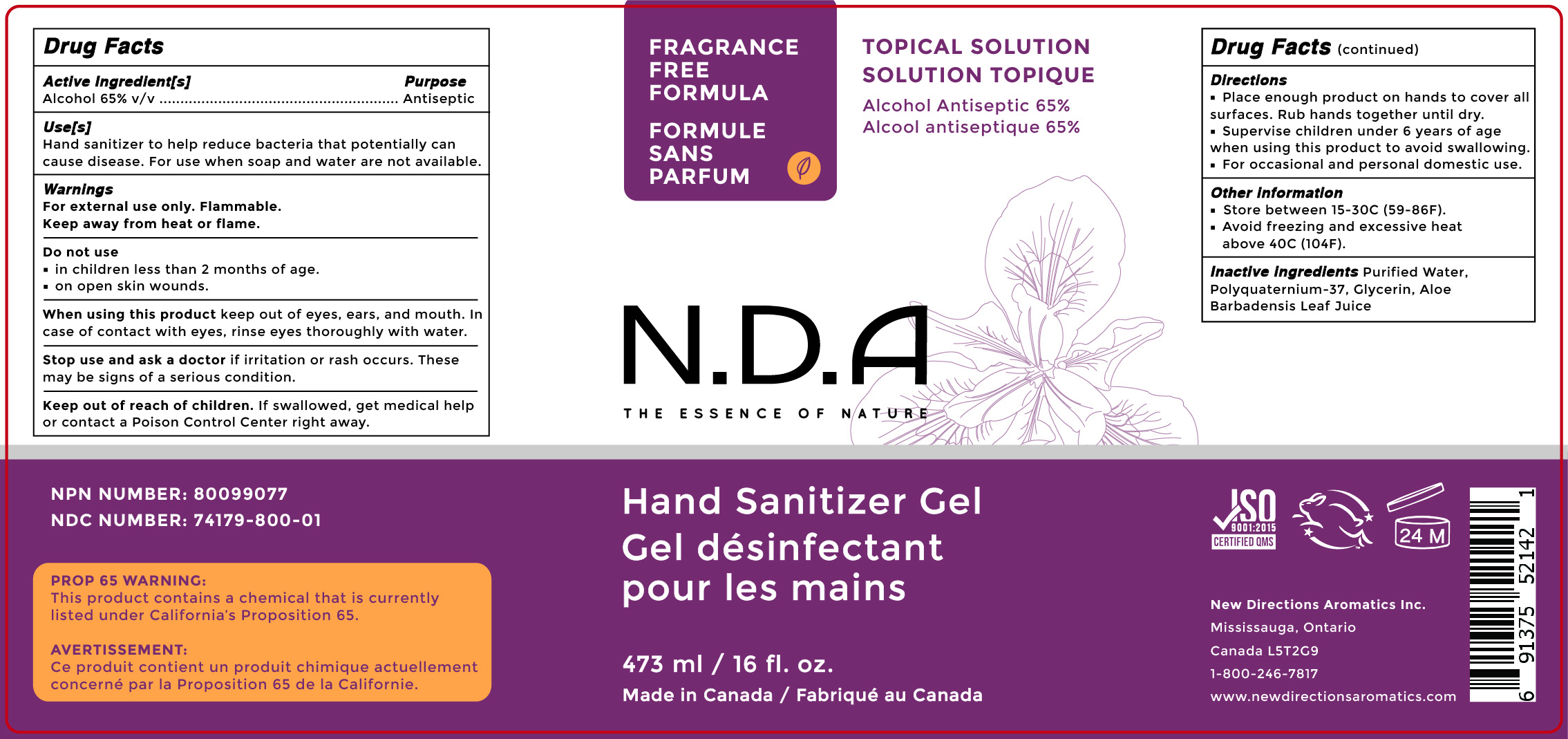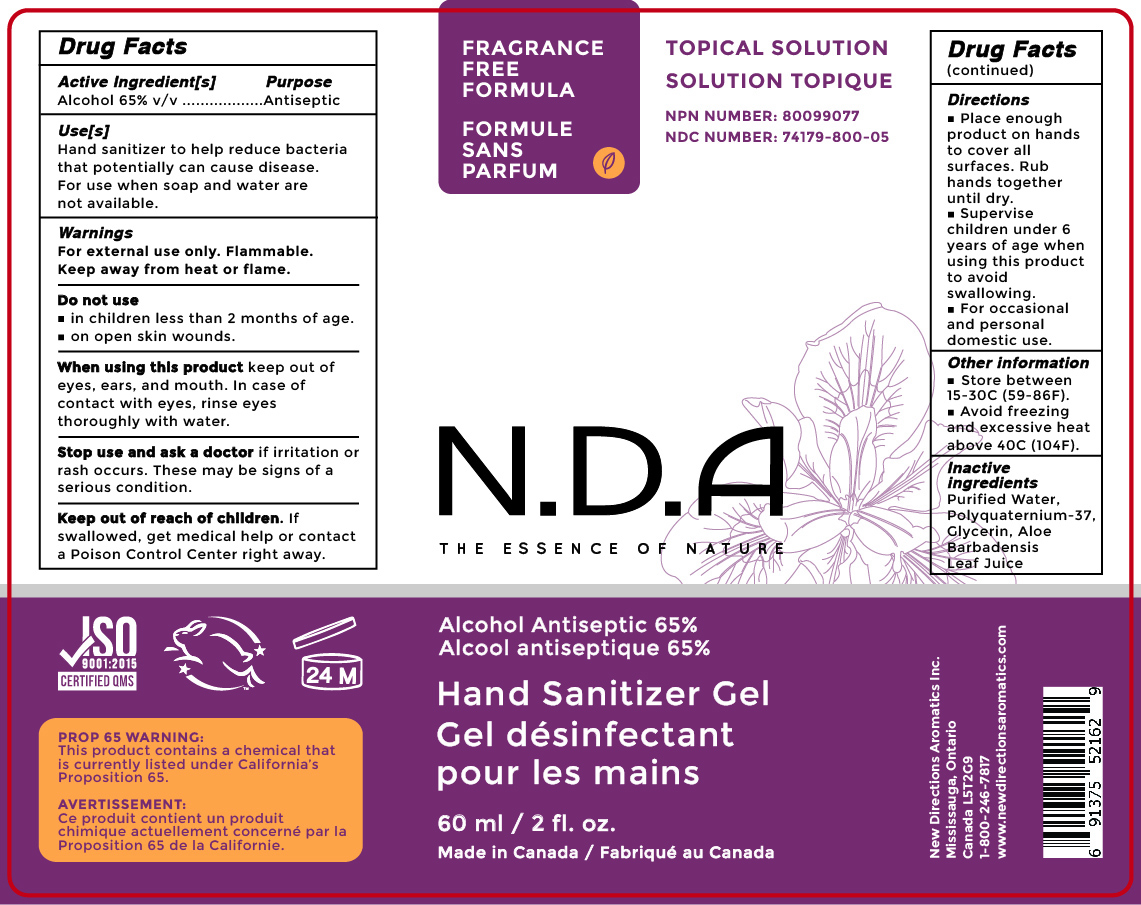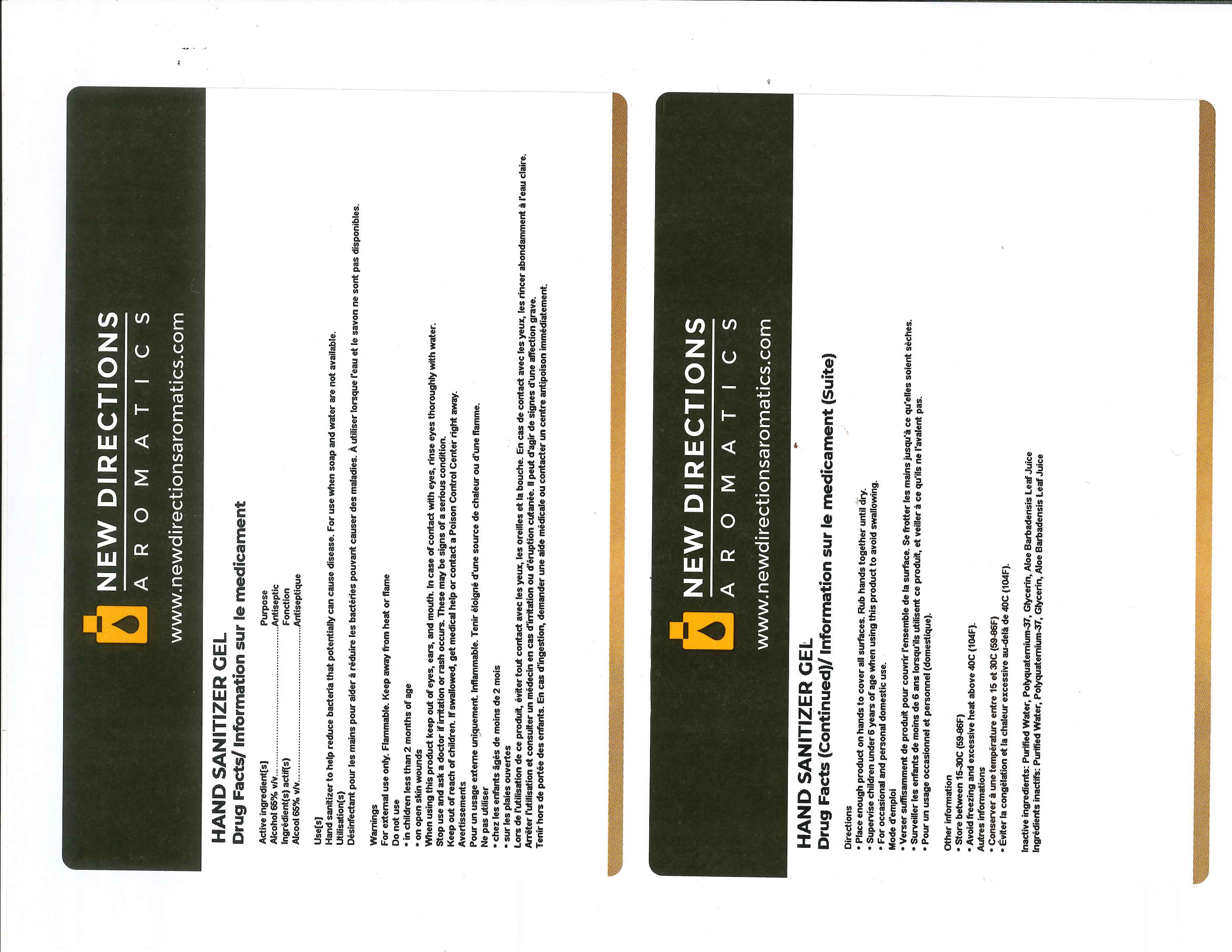 DRUG LABEL: Hand Sanitizer Gel
NDC: 74179-800 | Form: GEL
Manufacturer: New Directions Aromatics Inc.
Category: otc | Type: HUMAN OTC DRUG LABEL
Date: 20200721

ACTIVE INGREDIENTS: ALCOHOL 0.65 mL/1 mL
INACTIVE INGREDIENTS: WATER 0.33199 mL/1 mL; POLYQUATERNIUM-37 (25000 MPA.S) 0.008 mL/1 mL; ALOE VERA LEAF 0.00001 mL/1 mL; GLYCERIN 0.01 mL/1 mL

Hand Sanitizer Gel

ACTIVE INGREDIENT

Alcohol 65%. Purpose: Antiseptic

PURPOSE

Antiseptic, Hand Sanitizer

INDICATIONS AND USAGE

Hand Sanitizer to help reduce bacteria that potentially can cause disease. For use when soap and water are not available.

WARNINGS

For external use only. Flammable. Keep away from heat or flame.

This product contains a chemical that is currently listed under California's Proposition 65.

DO NOT USE

-In children less than 2 months of age.

-On open skin wounds

When using this product keep out of eyes, ears, and mouth. In case of contact with eyes, rinse eyes thoroughly with water.

Stop use and ask a doctor if irritation or rash occurs. These may be signs of a serious condition.

Keep out of reach of children. If swallowed, get medical help or contact a Poison Control Center right away.

DOSAGE AND ADMINISTRATION

Place enough product on hands to cover all surfaces. Rub hands together until dry.

Supervise children under 6 years of age when using this product to avoid swallowing.

STORAGE AND HANDLING

Store between 15-30C (59-86F)

Avoid freezing and excessive heat above 40C (104F)

INACTIVE INGREDIENT

Purified Water, Glycerin, Polyquaternium-37, Aloe Barbadensis Leaf Juice

PACKAGE LABEL

NDC 473 mL: 74179-800-01

NDC 200L: 74179-800-02

NDC 1000L: 74179-800-04

NDC 60 mL: 74179-800-05

NDC 240 mL: 74179-800-06